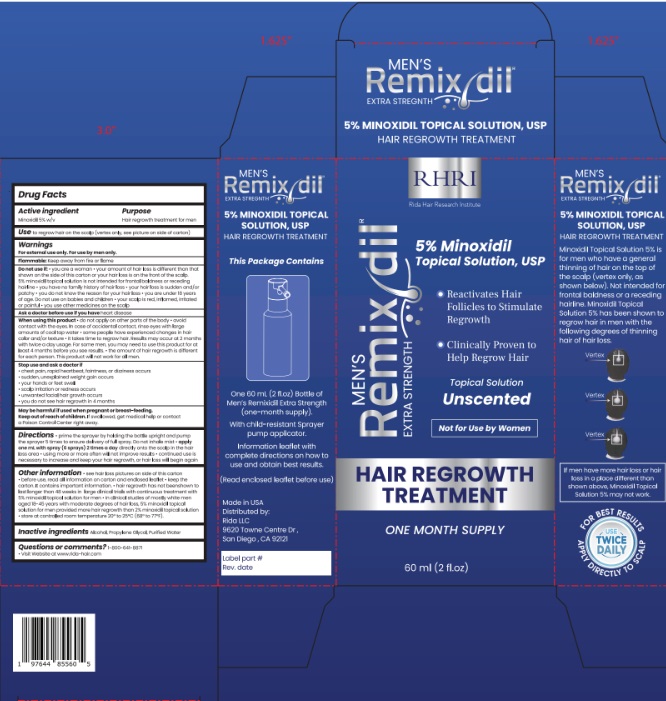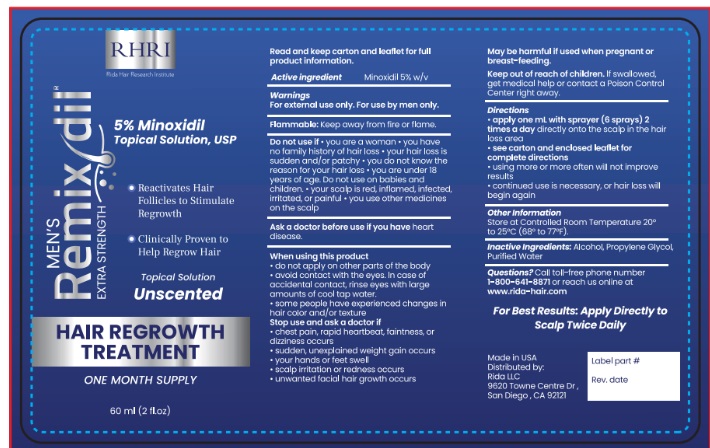 DRUG LABEL: Remixdil Extra Strength hair regrowth treatment for Men
NDC: 83004-008 | Form: SOLUTION
Manufacturer: Rida LLC
Category: otc | Type: HUMAN OTC DRUG LABEL
Date: 20250225

ACTIVE INGREDIENTS: MINOXIDIL 5 g/100 mL
INACTIVE INGREDIENTS: PROPYLENE GLYCOL; WATER; ISOPROPYL ALCOHOL

ACTIVE INGREDIENT

Minoxidil 5% w/v

PURPOSE

Hair regrowth treatment for men

USE

Use to regrow hair on the top of the scalp (vertex only, see pictures on side of carton)

WARNINGS

For external use only. For use by men only.

Flammable: Keep away from fire or flame

Do not use if

■ You are a woman

■ Your amount of hair loss is dierent than that shown on the side of this carton, or your hair loss is on the front of the scalp. 5% Minoxidil Topical Solution is not intended for frontal baldness or receding hairline.

■ You have no family history of hair loss

■ Your hair loss is sudden and/or patchy

■ You do not know the reason for your hair loss

■ You are under 18 years of age. Do not use on babies and children.

■ Your scalp is red, inflamed, infected, irritated, or painful

■ You use other medicines on the scalp

Ask a doctor before use if you have heart disease

When using this product

■ Do not apply on other parts of the body

■ Avoid contact with the eyes. In case of accidental contact, rinse eyes with large amounts of cool tap water.

■ Some people have experienced changes in hair color and/or texture

■ It takes time to regrow hair. Results may occur at 2 months with twice a day usage. For some men, you may need to use this product

for at least 4 months before you see results.

■ The amount of hair regrowth is different for each person. This product will not work for all men.

Stop use and ask a doctor if

■ Chest pain, rapid heartbeat, faintness, or dizziness occurs

■ Sudden, unexplained weight gain occurs

■ Your hands or feet swell

■ Scalp irritation or redness occurs

■ Unwanted facial hair growth occurs

■ You do not see hair regrowth in 4 months

Keep out of reach of children. If swallowed, get medical help or contact a Poison Control Center right away.

DOSAGE AND ADMINISTRATION

■ Apply one mL (6 sprays) 2 times a day directly onto the scalp in the area of hair loss

■ Using more or more often will not improve results

■ Continued use is necessary to increase and keep your hair regrowth, or hair loss will begin again.

OTHER SAFETY INFORMATION

- See hair loss pictures on side of this carton
- Before use, read all information on carton and enclosed leaflet
- Keep this carton. It contains important information.
- Hair regrowth has not been shown to last longer than 48 weeks in large clinical trials with continuous treatment with 5% minoxidil topical solution for men
- In clinical studies of mostly white men aged 18-19 years with moderate degrees of hair loss, 5% minoxidil topical solution for men provided more hair regrowth than 2% minoxidil topical solution
- Store at controlled room temperature between 68° - 77°F (20°-25°C).

INACTIVE INGREDIENT

Alcohol, Propylene Glycol, Purified Water

Questions or comments? 1-800-641-8871

Visit website at www.rida-hair.com

Keep out of reach of children. If swallowed, get medical help or contact a Poison Control Center right away.

PREGNANCY OR BREAST FEEDING

May be harmful if used when pregnant or breast-feeding.